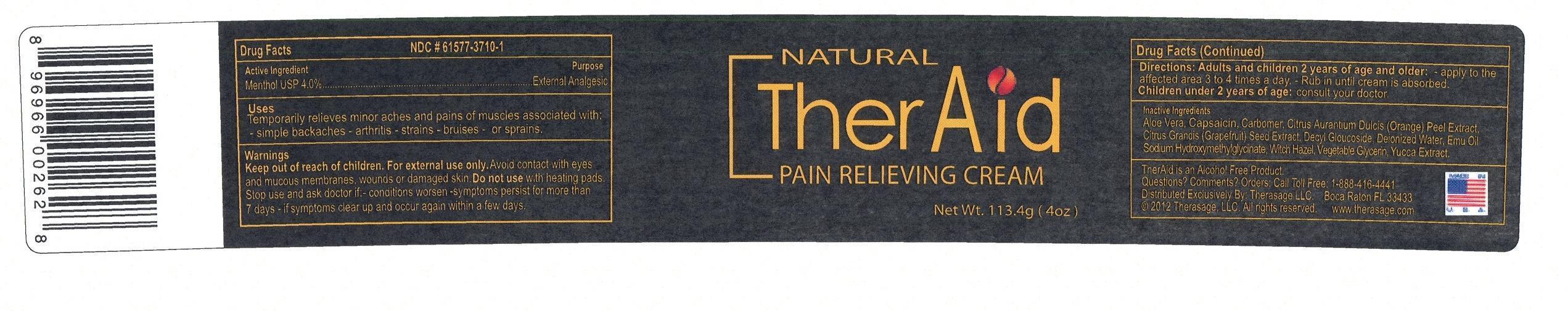 DRUG LABEL: THERAID
                
NDC: 61577-3710 | Form: GEL
Manufacturer: SOMBRA COSMETICS INC.
Category: otc | Type: HUMAN OTC DRUG LABEL
Date: 20130220

ACTIVE INGREDIENTS: MENTHOL .04 g/1 g
INACTIVE INGREDIENTS: ALOE VERA LEAF    ; CAPSICUM; CARBOMER HOMOPOLYMER TYPE C; DECYL GLUCOSIDE    ; WATER; GRAPEFRUIT SEED OIL    ; ORANGE PEEL    ; SODIUM HYDROXYMETHYLGLYCINATE    ; GLYCERIN; WITCH HAZEL    ; YUCCA SCHIDIGERA ROOT    ; EMU OIL

TherAid Natural Pain Relieving Cream

Active Ingredients

Menthol USP 4%

Purpose

External Analgesic

Keep out of reach of children

Uses

Temporarily relieves minor aches and pains of muscles and joints associated with: simple backaches, arthritis, strains, bruises, and sprains

Warnings

For external use only. Do not use on wounds or damaged skin. When using this product: avoid bandaging tightly, avoid contact with eyes, keep out of reach of children.

Stop use and ask doctor if: condition worsens, symptoms persist for more than 7 days, clear up and occur again within a few days.

Directions

adults and children 2 years of age and older: apply to affected area not more than 3 to 4 times daily, rub in thoroughly until gel is absorbed, children under 2 years of age: consult a doctor.

Inactive Ingredients

aloe vera extract, capsaicin, carbomer, decyl polyglucose, deionized water, emu oil, grapefruit seed extract, orange peel extract, sodium hydroxymethylglycinate, vegetable glycerin, witch hazel, yucca extract

Questions or Comments

1-888-416-4441

PACKAGE LABEL

theraid.jpg